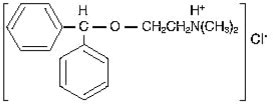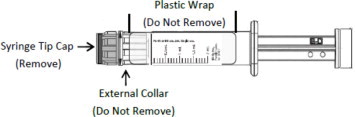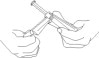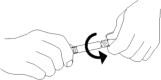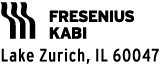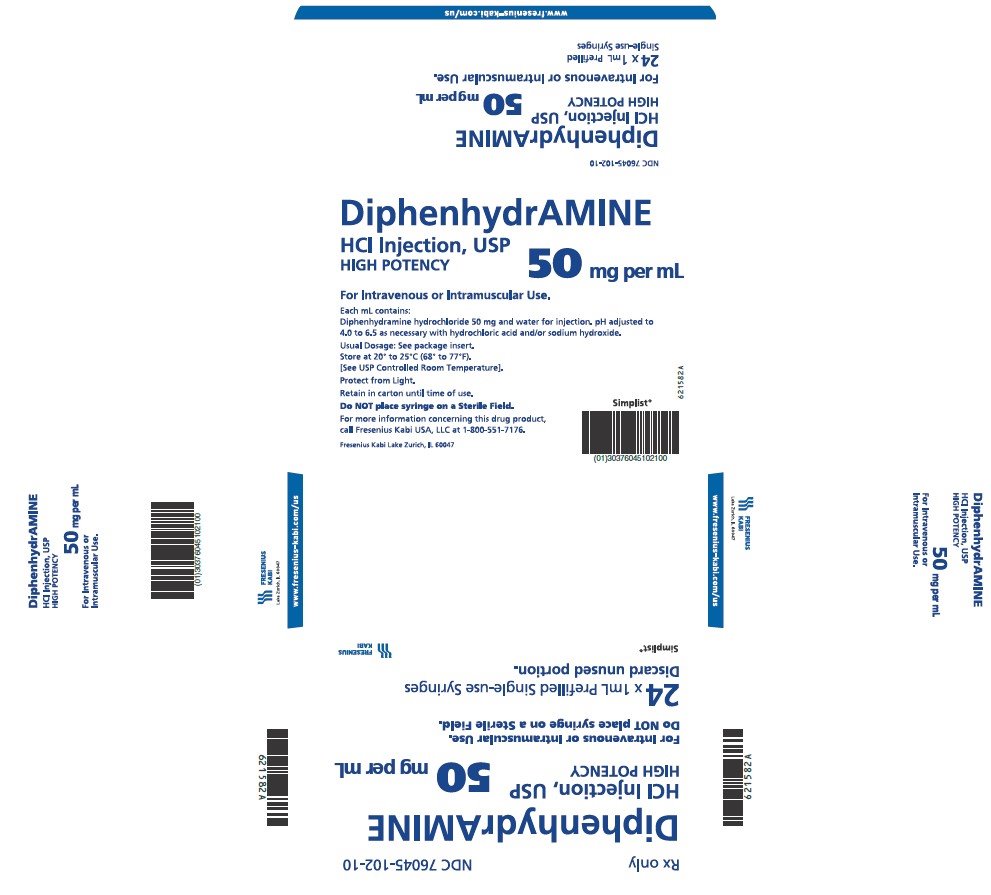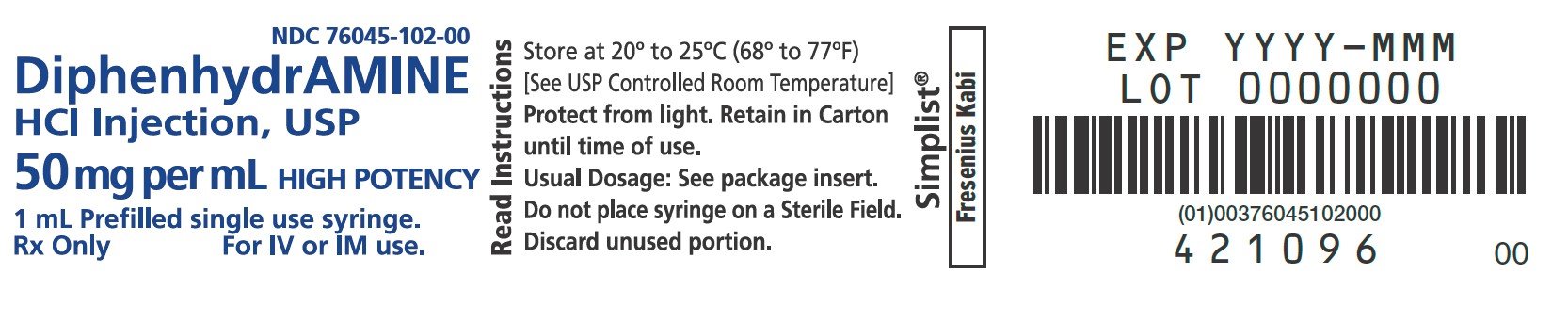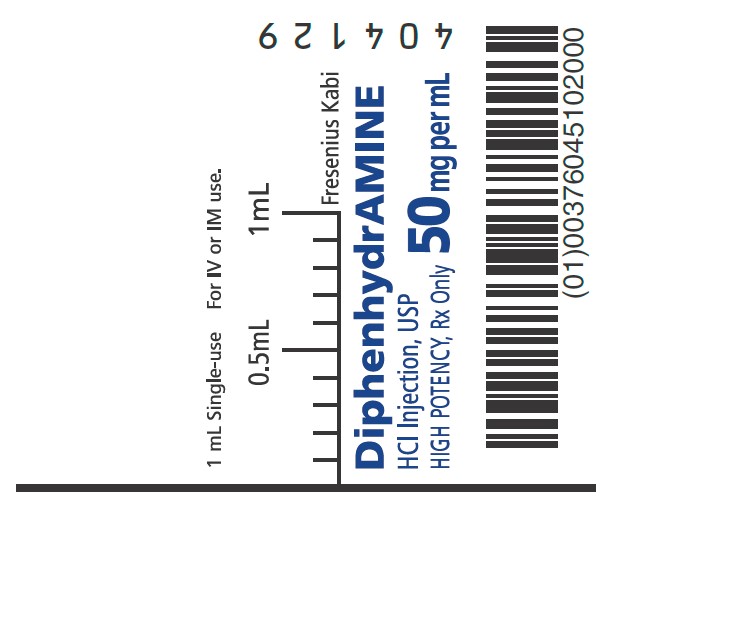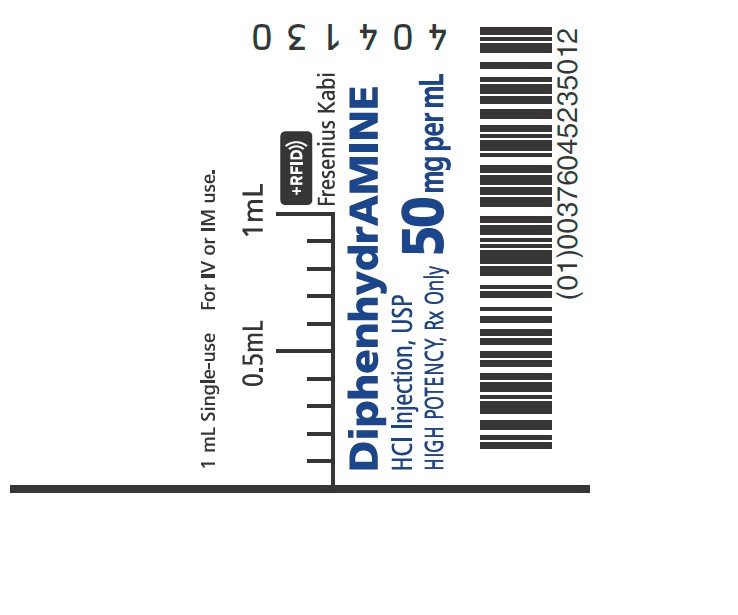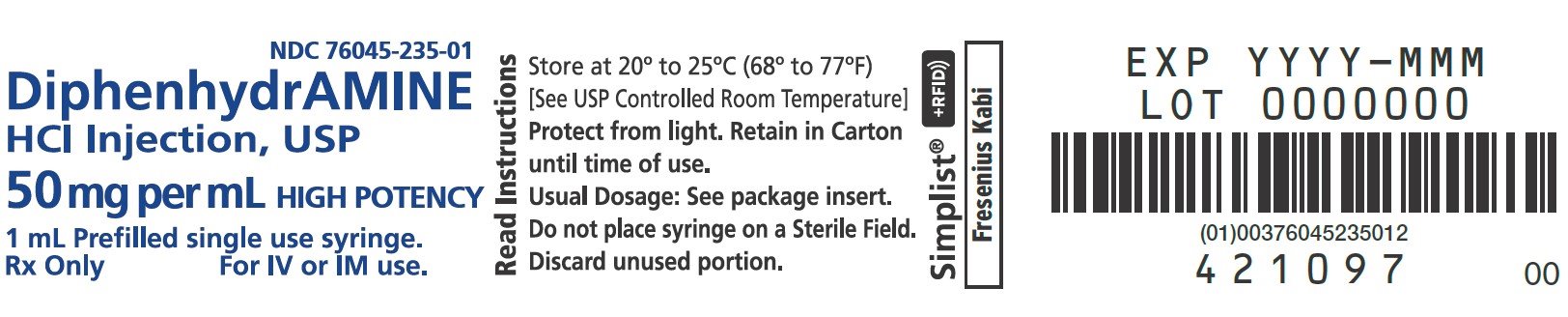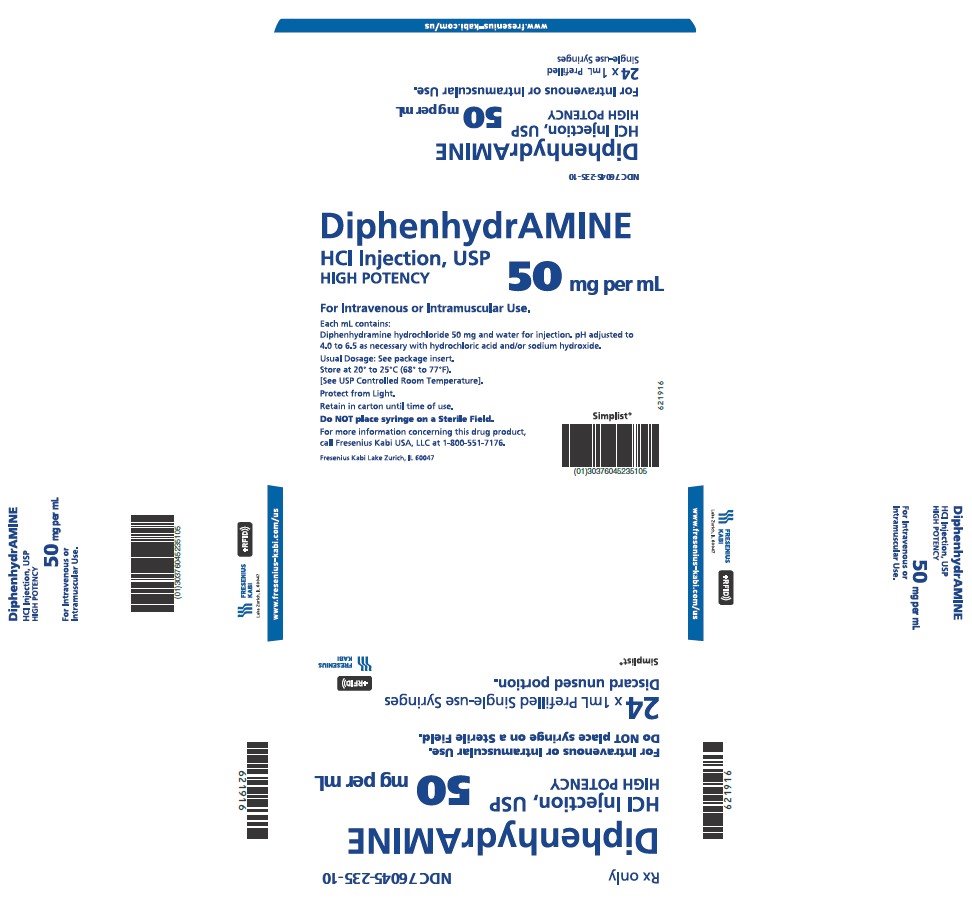 DRUG LABEL: Diphenhydramine Hydrochloride
NDC: 76045-102 | Form: INJECTION, SOLUTION
Manufacturer: Fresenius Kabi USA, LLC
Category: prescription | Type: HUMAN PRESCRIPTION DRUG LABEL
Date: 20250403

ACTIVE INGREDIENTS: DIPHENHYDRAMINE HYDROCHLORIDE 50 mg/1 mL
INACTIVE INGREDIENTS: SODIUM HYDROXIDE; HYDROCHLORIC ACID; WATER

DiphenhydrAMINE Hydrochloride Injection, USP

Rx Only

DESCRIPTION

Diphenhydramine hydrochloride is an antihistamine drug having the chemical name 2 (Diphenylmethoxy)-N,N-dimethylethylamine hydrochloride. It occurs as a white, crystalline powder, is freely soluble in water and alcohol and has a molecular weight of 291.82. The molecular formula is C 17H 21NO·HCl and the structural formula is as follows:

Diphenhydramine hydrochloride in the parenteral form is a sterile, pyrogen-free solution. Each mL contains a concentration of 50 mg of diphenhydramine hydrochloride and water for injection, for intramuscular or intravenous use. The solution for parenteral use has been adjusted to a pH between 4 and 6.5 with either sodium hydroxide or hydrochloric acid.

CLINICAL PHARMACOLOGY

Diphenhydramine hydrochloride is an antihistamine with anticholinergic (drying) and sedative side effects. Antihistamines appear to compete with histamine for cell receptor sites on effector cells.

Diphenhydramine hydrochloride in the injectable form has a rapid onset of action. Diphenhydramine hydrochloride is widely distributed throughout the body, including the CNS. A portion of the drug is excreted unchanged in the urine, while the rest is metabolized via the liver. Detailed information on the pharmacokinetics of Diphenhydramine Hydrochloride Injection is not available.

INDICATIONS AND USAGE

Diphenhydramine hydrochloride in the injectable form is effective in adults and pediatric patients, other than premature infants and neonates, for the following conditions when diphenhydramine hydrochloride in the oral form is impractical.

Antihistaminic: For amelioration of allergic reactions to blood or plasma, in anaphylaxis as an adjunct to epinephrine and other standard measures after the acute symptoms have been controlled, and for other uncomplicated allergic conditions of the immediate type when oral therapy is impossible or contraindicated.

Motion Sickness: For active treatment of motion sickness.

Antiparkinsonism: For use in parkinsonism, when oral therapy is impossible or contraindicated, as follows: parkinsonism in the elderly who are unable to tolerate more potent agents; mild cases of parkinsonism in other age groups, and in other cases of parkinsonism in combination with centrally acting anticholinergic agents.

CONTRAINDICATIONS

Use in Neonates or Premature Infants: This drug should not be used in neonates or premature infants.

Use in Nursing Mothers: Because of the higher risk of antihistamines for infants generally, and for neonates and prematures in particular, antihistamine therapy is contraindicated in nursing mothers.

Use as a Local Anesthetic: Because of the risk of local necrosis, this drug should not be used as a local anesthetic.

Antihistamines are also contraindicated in the following conditions: Hypersensitivity to diphenhydramine hydrochloride and other antihistamines of similar chemical structure.

WARNINGS

Antihistamines should be used with considerable caution in patients with narrow-angle glaucoma, stenosing peptic ulcer, pyloroduodenal obstruction, symptomatic prostatic hypertrophy, or bladder-neck obstruction.

Local necrosis has been associated with the use of subcutaneous or intradermal use of intravenous diphenhydramine.

Use in Pediatric Patients: In pediatric patients, especially, antihistamines in overdosage may cause hallucinations, convulsions, or death.

As in adults, antihistamines may diminish mental alertness in pediatric patients. In the young pediatric patient, particularly, they may produce excitation.

Use in the Elderly (approximately 60 years or older): Antihistamines are more likely to cause dizziness, sedation, and hypotension in elderly patients.

PRECAUTIONS

GENERAL PRECAUTIONS

General: Diphenhydramine hydrochloride has an atropine-like action and, therefore should be used with caution in patients with a history of bronchial asthma, increased intraocular pressure, hyperthyroidism, cardiovascular disease or hypertension. Use with caution in patients with lower respiratory disease including asthma.

PATIENT COUNSELING INFORMATION

Information for Patients: Patients taking diphenhydramine hydrochloride should be advised that this drug may cause drowsiness and has an additive effect with alcohol.

Patients should be warned about engaging in activities requiring mental alertness such as driving a car or operating appliances, machinery, etc.

DRUG INTERACTIONS

Drug Interactions: Diphenhydramine hydrochloride has additive effects with alcohol and other CNS depressants (hypnotics, sedatives, tranquilizers, etc).

MAO inhibitors prolong and intensify the anticholinergic (drying) effects of antihistamines.

CARCINOGENESIS AND MUTAGENESIS AND IMPAIRMENT OF FERTILITY

Carcinogenesis, Mutagenesis, Impairment of Fertility: Long-term studies in animals to determine mutagenic and carcinogenic potential have not been performed.

PREGNANCY

Pregnancy: Pregnancy Category B: Reproduction studies have been performed in rats and rabbits at doses up to 5 times the human dose and have revealed no evidence of impaired fertility or harm to the fetus due to diphenhydramine hydrochloride. There are, however, no adequate and well-controlled studies in pregnant women. Because animal reproduction studies are not always predictive of human response, this drug should be used during pregnancy only if clearly needed.

PEDIATRIC USE

Pediatric Use: Diphenhydramine should not be used in neonates and premature infants (see CONTRAINDICATIONS).

Diphenhydramine may diminish mental alertness, or in the young pediatric patient, cause excitation. Overdosage may cause hallucinations, convulsions, or death (see WARNINGS and OVERDOSAGE).

See also DOSAGE AND ADMINISTRATION section.

ADVERSE REACTIONS

The most frequent adverse reactions are underscored:

1. General: Urticaria, drug rash, anaphylactic shock, photosensitivity, excessive perspiration, chills, dryness of mouth, nose, and throat.
2. Cardiovascular System: Hypotension, headache, palpitations, tachycardia, extrasystoles.
3. Hematologic System: Hemolytic anemia, thrombocytopenia, agranulocytosis.
4. Nervous System: Sedation, sleepiness, dizziness, disturbed coordination, fatigue, confusion, restlessness, excitation, nervousness, tremor, irritability, insomnia, euphoria, paresthesia, blurred vision, diplopia, vertigo, tinnitus, acute labyrinthitis, neuritis, convulsions.
5. GI System: Epigastric distress, anorexia, nausea, vomiting, diarrhea, constipation.
6. GU System: Urinary frequency, difficult urination, urinary retention, early menses.
7. Respiratory System: Thickening of bronchial secretions, tightness of chest or throat and wheezing, nasal stuffiness.

OVERDOSAGE

Antihistamine overdosage reactions may vary from central nervous system depression to stimulation. Stimulation is particularly likely in pediatric patients. Atropine-like signs and symptoms; dry mouth; fixed, dilated pupils; flushing; and gastrointestinal symptoms may also occur.

Stimulants should not be used.

Vasopressors may be used to treat hypotension.

DOSAGE AND ADMINISTRATION

THIS PRODUCT IS FOR INTRAVENOUS OR INTRAMUSCULAR ADMINISTRATION ONLY.

Diphenhydramine hydrochloride in the injectable form is indicated when the oral form is impractical.

Parenteral drug products should be inspected visually for particulate matter and discoloration prior to administration, whenever solution and container permit.

DOSAGE SHOULD BE INDIVIDUALIZED ACCORDING TO THE NEEDS AND THE RESPONSE OF THE PATIENT.

Pediatric Patients, other than premature infants and neonates: 5 mg/kg/24 hr or 150 mg/m ^2/24 hr. Maximum daily dosage is 300 mg. Divide into four doses, administered intravenously at a rate generally not exceeding 25 mg/min, or deep intramuscularly.

Adults: 10 mg to 50 mg intravenously at a rate generally not exceeding 25 mg/min, or deep intramuscularly, 100 mg if required; maximum daily dosage is 400 mg.

HOW SUPPLIED

Diphenhydramine Hydrochloride Injection, USP is a clear and colorless solution available as:

Product Code | Unit of Sale | Strength | Each
RF787210 | NDC 76045-235-10 Unit of 24 | 50 mg/mL in a 1 mL Prefilled Single-Use Syringe | NDC 76045-235-01 1 mL Prefilled Single-Use Syringe This Product Contains an RFID.
787210 | NDC 76045-102-10 Unit of 24 | 50 mg/mL in a 1 mL Prefilled Single-Use Syringe | NDC 76045-102-00 1 mL Prefilled Single-Use Syringe

Store at 20° to 25°C (68° to 77°F) [See USP Controlled Room Temperature.]

Protect from freezing and light. Retain in carton until time of use.

Do not place syringe on a sterile field.

INSTRUCTIONS FOR USE

CAUTION: Certain glass syringes may malfunction, break or clog when connected to some Needleless Luer Access Devices (NLADs) and needles. This syringe has a larger internal syringe tip and an external collar (luer collar). The external collar must remain attached to the syringe. Data show that the syringe achieves acceptable connections with the BD Eclipse™ Needle and the Terumo SurGuard2™ Safety Needle and with the following non-center post NLADs: Alaris SMARTSITE™, B-Braun ULTRASITE™, BD-Q SYTE™, Maximum MAX PLUS™, and B-Braun SAFSITE™. The data also show acceptable connections are achieved to the center post ICU Medical CLAVE™. However, spontaneous disconnection of this glass syringe from needles and NLADs with leakage of drug product may occur. Assure that the needle or NLAD is securely attached before beginning the injection. Visually inspect the glass syringe-needle or glass syringe –NLAD connection before and during drug administration. Do not remove the clear plastic wrap around the external collar. (See Figure 1)

Figure 1

1. Inspect the outer packaging (blister pack) by verifying:
  1. blister integrity
  2. drug name
  3. drug strength
  4. dose volume
  5. route of administration
  6. expiration date to be sure that the drug has not expired
  7. sterile field applicability
Do not use if package has been damaged.
2. Peel open the paper (top web) of the outer packaging that displays the product information to access the syringe. Do not pop syringe through.
3. Bend the plastic part of the outer packaging (thermoform) so as to present the plunger rod for syringe removal. (See Figure 2)
Figure 2
4. Perform visual inspection on the syringe by verifying:
  1. absence of syringe damage
  2. absence of external particles
  3. absence of internal particles
  4. proper drug color
  5. expiration date to be sure that the drug has not expired
  6. drug name
  7. drug strength
  8. dose volume
  9. route of administration
  10. integrity of the plastic wrap around the external collar
5. Do not remove plastic wrap around the external collar. Push plunger rod slightly to break the stopper loose while tip cap is still on.
6. Do not remove plastic wrap around the external collar. Remove tip cap by twisting it off. (See Figure 3)
Figure 3
7. Discard the tip cap.
8. Expel air bubble.
9. Adjust dose into sterile material (if applicable).
10. Connect the syringe to appropriate injection connection depending on route of administration. Before injection, ensure that the syringe is securely attached to the needle or needleless luer access device (NLAD).
11. Depress plunger rod to deliver medication. Ensure that pressure is maintained on the plunger rod during the entire administration.
12. Remove syringe from NLAD (if applicable) and discard into appropriate receptacle. If delivering the medication with a needle, to prevent needle stick injuries, do not recap needle.
NOTES:
17. - All steps must be done sequentially
18. - Do not autoclave syringe
19. - Do not use this product on a sterile field
20. - Do not introduce any other fluid into the syringe at any time
21. - This product is for single dose only
For more information concerning this drug, please call Fresenius Kabi USA, LLC at 1-800-551-7176.
To report SUSPECTED ADVERSE REACTIONS, contact Fresenius Kabi USA, LLC at 1-800-551-7176 or FDA at 1-800-FDA-1088 or www.fda.gov/medwatch.
The brand names mentioned in this document are the trademarks of their respective owners.

www.fresenius-kabi.com/us

451609A
Revised: November 2024

PACKAGE LABEL - PRINCIPAL DISPLAY – Diphenhydramine 1 mL Carton

Rx only NDC 76045-102-10

DiphenhydrAMINE

HCl Injection, USP

HIGH POTENCY 50 mg per mL
For Intravenous or Intramuscular Use.

Do NOT place syringe on a Sterile Field.
24 x 1mL Prefilled
Single-use Syringes
Discard unused portion.

PACKAGE LABEL - PRINCIPAL DISPLAY – Diphenhydramine 1 mL Blister Pack Label

NDC 76045-102-00
DiphenhydrAMINE

HCl Injection, USP

50 mg per mL HIGH POTENCY

1 mL Prefilled single use syringe.

Rx Only For IV or IM use.

PACKAGE LABEL - PRINCIPAL DISPLAY – Diphenhydramine 1 mL Syringe Label

1 mL Single-use For IV or IM use.

DiphenhydrAMINE

HCl Injection, USP
HIGH POTENCY, Rx Only 50 mg per mL

PACKAGE LABEL - PRINCIPAL DISPLAY – Diphenhydramine 1 mL Blister Pack Label

NDC 76045-235-01

DiphenhydrAMINE

HCl Injection, USP

50 mg per mL HIGH POTENCY

1 mL Prefilled single use syringe.

Rx Only For IV or IM use.

PACKAGE LABEL - PRINCIPAL DISPLAY – Diphenhydramine 1 mL Carton

Rx only NDC 76045-235-10

DiphenhydrAMINE

HCl Injection, USP

HIGH POTENCY 50 mg per mL

For Intravenous or Intramuscular Use.

Do NOT place syringe on a Sterile Field.

24 x 1mL Prefilled
Single-use Syringes

Discard unused portion.